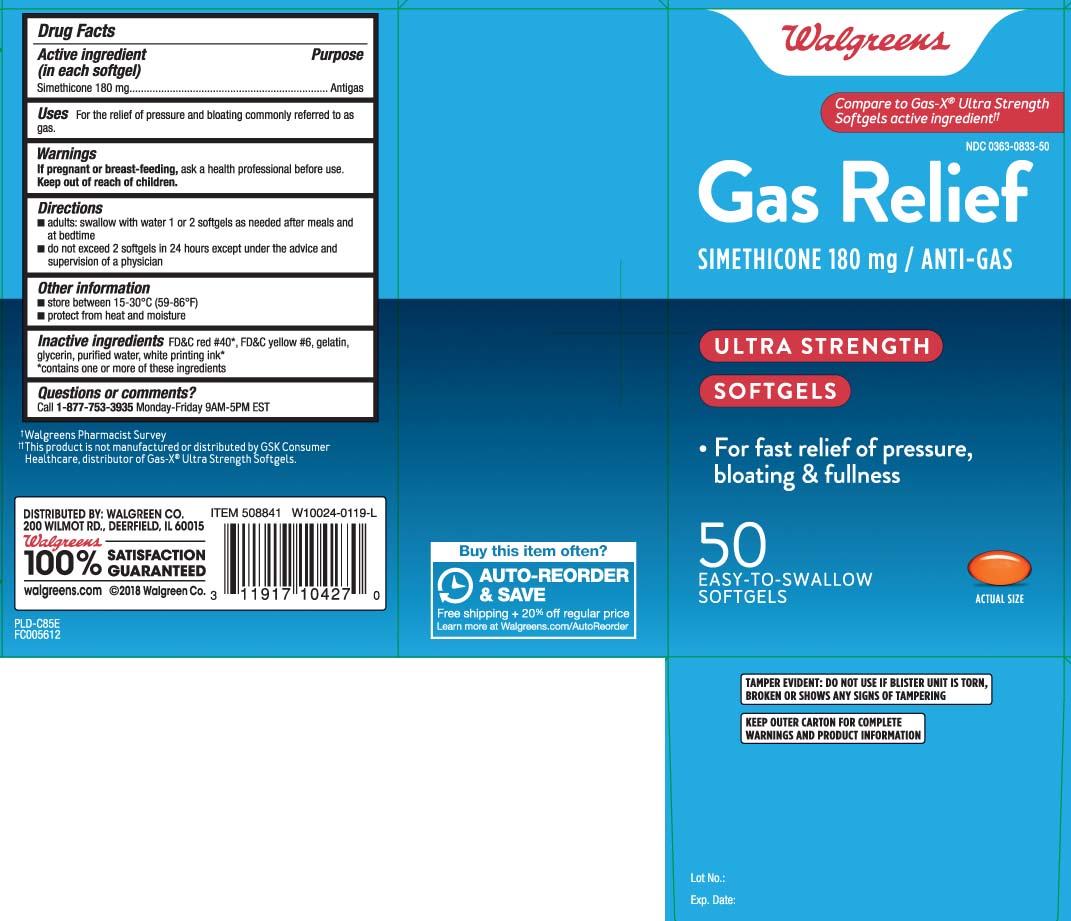 DRUG LABEL: Gas Relief
NDC: 0363-0833 | Form: CAPSULE, LIQUID FILLED
Manufacturer: Walgreens
Category: otc | Type: HUMAN OTC DRUG LABEL
Date: 20240626

ACTIVE INGREDIENTS: DIMETHICONE 180 mg/1 1
INACTIVE INGREDIENTS: FD&C YELLOW NO. 6; FD&C RED NO. 40; GELATIN; GLYCERIN; WATER

Drug Facts

Active ingredient (in each softgel)

Simethicone 180 mg

Purpose

Antigas

Uses

for the relief of pressure, bloating, and fullness commonly referred to as gas

Warnings

If pregnant or breast-feeding,

ask a health professional before use.

Directions

- adults: swallow with water 1 or 2 softgels as needed after meals and at bedtime
- do not exceed 2 softgels in 24 hours except under the advice and supervision of a physican

Other information

- store between 15-30°C (59-86°F)
- protect from light, heat, and moisture

Inactive ingredients

FD&C red #40*, FD&C yellow #6, gelatin, glycerin, purified water, white printing ink*

*contain one or more of these ingredients

Questions or comments?

Call 1-877-753-3935 Monday-Friday 9AM-5PM EST

Principal Display Panel

Compare to Gas-X® Ultra Strength Softgels active ingredient††

Gas Relief

SIMETHICONE 180 mg / ANTI-GAS

ULTRA STRENGTH

SOFTGELS

- For fast relief of pressure, bloating & fullness

EASY-TO-SWALLOW

SOFTGELS

TAMPER EVIDENT: DO NOT USE IF BLISTER UNIT IS TORN, BROKEN OR SHOWS ANY SIGNS OF TAMPERING.

KEEP OUTER CARTON FOR COMPLETE WARNINGS AND PRODUCT INFORMATION.

††This product is not manufactured or distributed by GSK Consumer Healthcare, distributor of Gas- X® Ultra Strength Softgels.

DISTRIBUTED BY: WALGREEN CO.

200 WILMOT RD., DEERFIELD, IL 60015

walgreens.com

Product Label

WALGREENS Gas Relief 180 mg